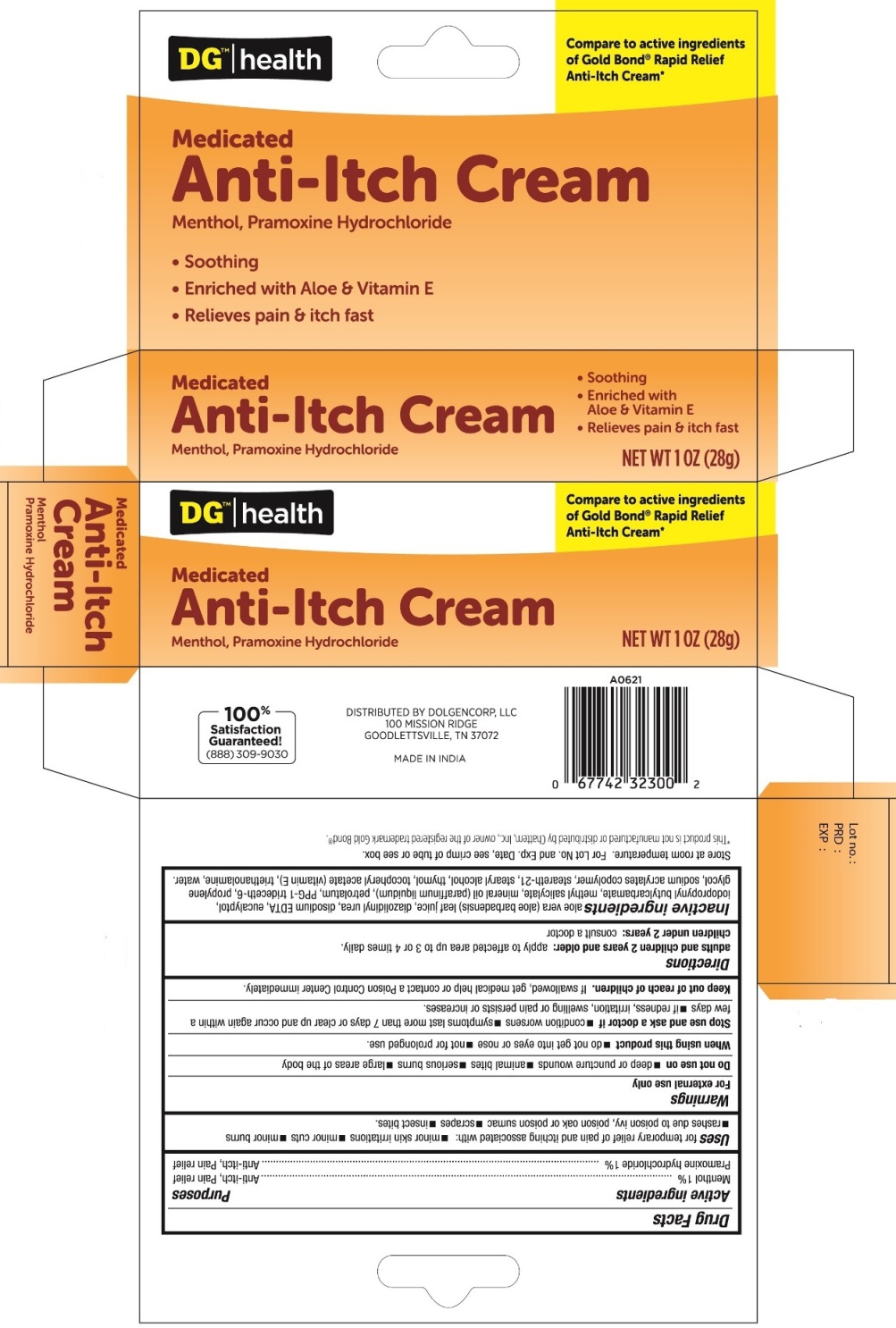 DRUG LABEL: Anti-Itch
NDC: 55910-407 | Form: CREAM
Manufacturer: Dolgencorp, Inc.
Category: otc | Type: HUMAN OTC DRUG LABEL
Date: 20160701

ACTIVE INGREDIENTS: MENTHOL 1 g/100 g; PRAMOXINE HYDROCHLORIDE 1 g/100 g
INACTIVE INGREDIENTS: ALOE VERA LEAF; DIAZOLIDINYL UREA; EDETATE DISODIUM; EUCALYPTOL; IODOPROPYNYL BUTYLCARBAMATE; METHYL SALICYLATE; MINERAL OIL; PETROLATUM; PPG-1 TRIDECETH-6; PROPYLENE GLYCOL; STEARETH-21; STEARYL ALCOHOL; THYMOL; .ALPHA.-TOCOPHEROL ACETATE; TROLAMINE; WATER

Anti-Itch

Active ingredients

Menthol 1%

Pramoxine hydrochloride 1%

Purpose

Anti-itch, Pain relief

Uses

for temporary relief of pain and itching associated with:

- minor skin irritations
- minor cuts
- minor burns
- rashes due to poison ivy, poison oak or poison sumac
- scrapes
- insect bites

Warnings

For external use only

Do not use on

- deep or puncture wounds
- animals bites
- serious burns
- large areas of the body

When using this product

- do not get into eyes or nose
- not for prolonged use

Stop use and ask a doctor if

- condition worsens
- symptoms last more than 7 days or clear up and occur again within a few days
- if redness, irritation, swelling or pain persists or increases

Keep out of reach of children.

If swallowed, get medical help or contact a Poison Control Center immediately.

Directions

adults and children 2 years and older: apply to affected area up to 3 or 4 times daily

children under 2 years: consult a doctor

Inactive ingredients

aloe vera (aloe barbadensis) leaf juice, diazolidinyl urea, disodium EDTA, eucalyptol, iodopropynyl butylcarbamate, methyl salicylate, mineral oil (parraffinum liquidum), petrolatum, PPG-1 trideceth-6, propylene glycol, sodium acrylates copolymer, steareth-21, stearyl alcohol, thymol, tocopheryl acetate (vitamin E), triethanolamine, water

Other information

- store at room temperature
- for lot no. and exp. date, see crimp of tube or see box

PACKAGE LABEL

PRINCIPAL DISPLAY PANEL

ANTI-ITCH CREAM

NET WT 1 OZ (28 g)